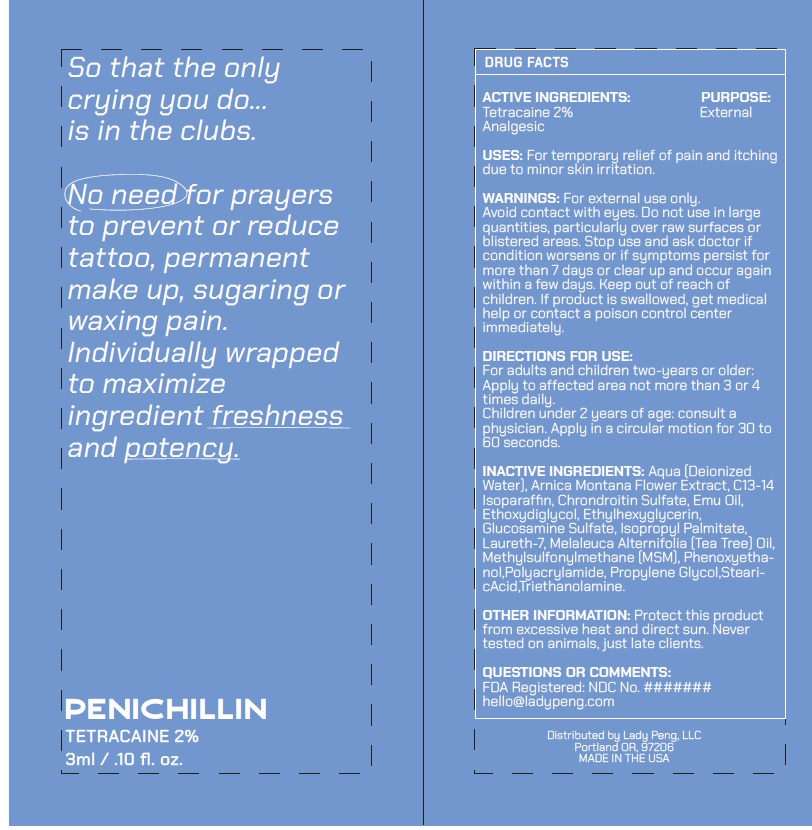 DRUG LABEL: PENICHILLIN
NDC: 54723-014 | Form: CREAM
Manufacturer: Sambria Pharmaceuticals, LLC
Category: otc | Type: HUMAN OTC DRUG LABEL
Date: 20230817

ACTIVE INGREDIENTS: TETRACAINE 2 g/100 mL
INACTIVE INGREDIENTS: WATER; ARNICA MONTANA FLOWER; C13-14 ISOPARAFFIN; CHONDROITIN SULFATE (BOVINE); EMU OIL; DIETHYLENE GLYCOL MONOETHYL ETHER; ETHYLHEXYLGLYCERIN; GLUCOSAMINE SULFATE; ISOPROPYL PALMITATE; LAURETH-7; TEA TREE OIL; DIMETHYL SULFONE; PHENOXYETHANOL; POLYACRYLAMIDE (CROSSLINKED; 2 MOLE PERCENT BISACRYLAMIDE); PROPYLENE GLYCOL; STEARIC ACID; TROLAMINE

Active ingredient

Tetracaine 2%

Purpose

External Analgesic

Uses

For temporary relief of pain and itching due to minor skin irritation.

Warnings

For external use only. Avoid contact with eyes. Do not use in large quantities, particularly over raw surfaces or blistered areas.

Stop use and ask doctor if condition worsens or if symptoms persist for more than 7 days or clear up and occur again within a few days.

Keep out of reach of children. If product is swallowed, get medical help or contact a poison control center immediately.

Keep out of reach of children

If swallowed, get medical help or contact a Poison Control Center right away.

Directions

For adults and children two-years or older: Apply to affected area not more than 3 or 4 times daily.

Children under 2 years of age: consult a physician. Apply in a circular motion for 30 to 60 seconds.

Inactive ingredients

Aqua (Deionized Water), Arnica Montana Flower Extract, C13-14 Isoparaffin, Chrondroitin Sulfate, Emu Oil, Ethoxydiglycol, Ethylhexyglycerin,
Glucosamine Sulfate, Isopropyl Palmitate, Laureth-7, Melaleuca Alternifolia (Tea Tree) Oil, Methylsulfonylmethane (MSM), Phenoxyethanol,
Polyacrylamide, Propylene Glycol,StearicAcid, Triethanolamine.

Other information

Protect this product from excessive heat and direct sun. Never tested on animals, just late clients.